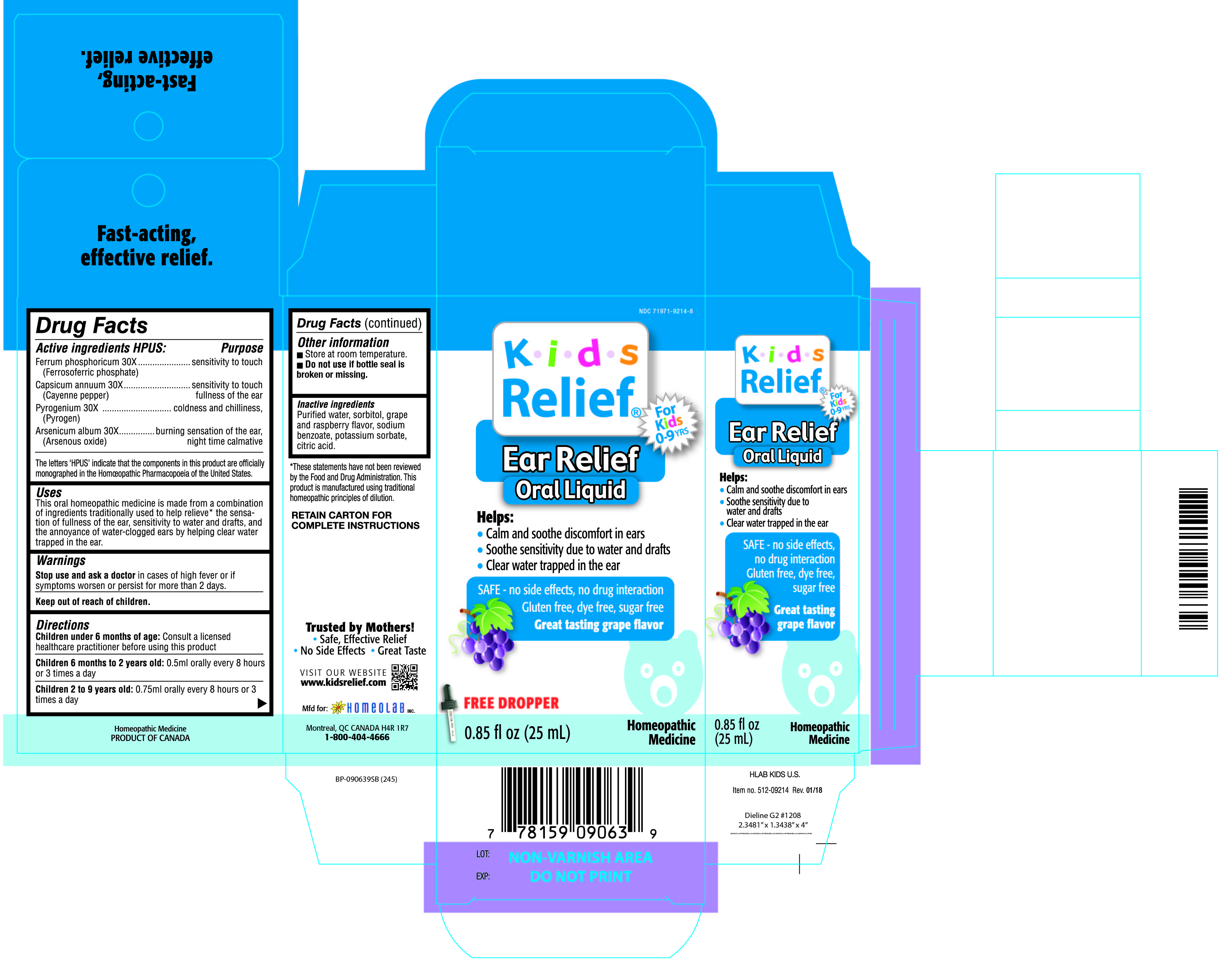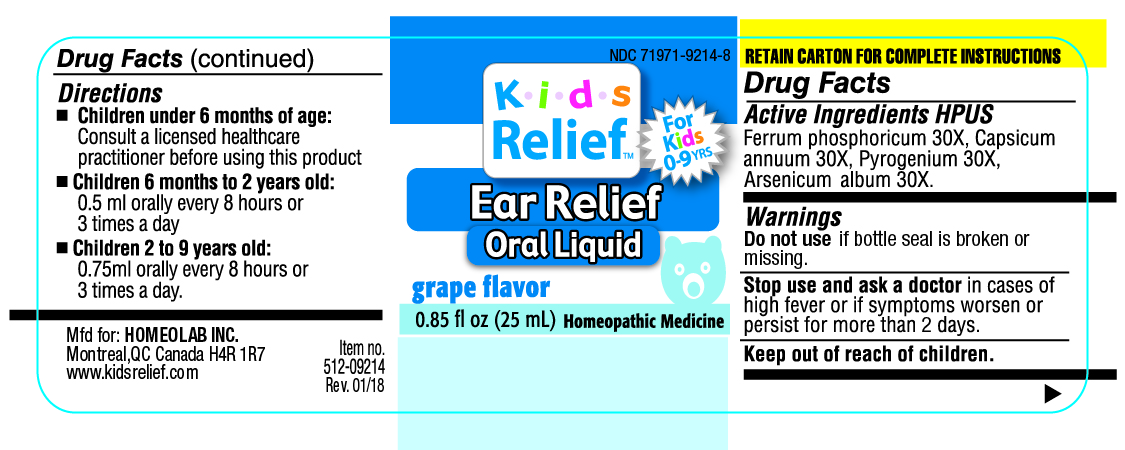 DRUG LABEL: Kids Relief
NDC: 71971-9214 | Form: LIQUID
Manufacturer: Homeolab International (Canada) inc
Category: homeopathic | Type: HUMAN OTC DRUG LABEL
Date: 20190716

ACTIVE INGREDIENTS: FERRUM PHOSPHORICUM 30 [hp_X]/25 mL; capsicum 30 [hp_X]/25 mL; RANCID BEEF 30 [hp_X]/25 mL; ARSENIC TRIOXIDE 30 [hp_X]/25 mL
INACTIVE INGREDIENTS: WATER; SORBITOL; SODIUM BENZOATE; POTASSIUM SORBATE; CITRIC ACID MONOHYDRATE

Active ingredients HPUS:

Ferrum phosphoricum 30X

(Ferrosoferic phosphate)

Capsicum annuum 30X

(Cayenne pepper)

Pyrogenium 30X

(Pyrogen)

Arsenicum album 30X

(Arsenous oxide)

The letters 'HPUS' indicate that the component in this product is officially

monographed in the Homeopathic Pharmacopoeia of the United States)

Purpose

Ferrum phosphoricum 30X ..............sensitivity to touch

(Ferrosoferic phosphate)

Capsicum annuum 30X ...................sensitivity to touch fullness of the ear

(Cayenne pepper)

Pyrogenium 30X ............................coldness and chilliness,

(Pyrogen)

Arsenicum album 30X ....................burning sensation of the ear, night time calmative

(Arsenous oxide)

Uses

This oral homeopathic medicine is made from a combination

of ingredients traditionally used to help relieve* the sensa-

tion of fullness of the ear, sensitivity to water and drafts, and

the annoyance of water-clogged ears by helping clear water

trapped in the ear.

Warnings

Stop use and ask a doctor in cases of high fever or if

symptoms worsen or persist for more than 2 days.

Keep out of reach of children.

Directions

Children under 6 months of age: Consult a licensed

healthcare practitioner before using this product

Children 6 months to 2 years old: 0.5 ml orally every 8 hours

or 3 times a day

Children 2 to 9 years old: 0.75 ml orally every 8 hours or 3

times a day

Other information

•Store at room temperature

•Do not use if bottle seal is

broken or missing.

Inactive ingredients

Purified water, sorbitol, grape

and raspberry flavor, sodium

benzoate, potassium sorbate,

citric acid.